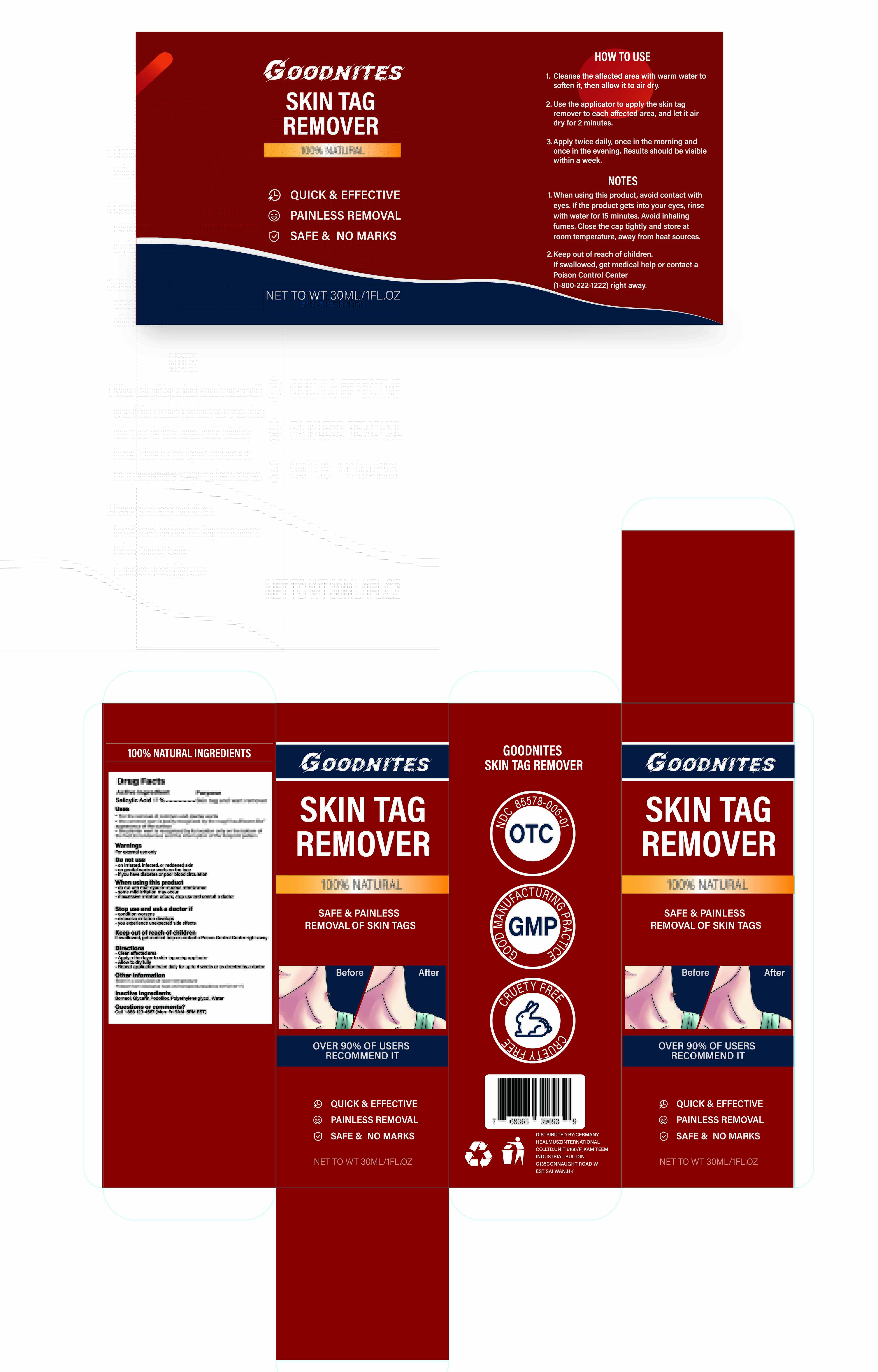 DRUG LABEL: Goodnites Skin tag and wart remover
NDC: 85578-006 | Form: LIQUID
Manufacturer: Zhengzhou Hangrui Network Technology Co., Ltd.
Category: otc | Type: HUMAN OTC DRUG LABEL
Date: 20250724

ACTIVE INGREDIENTS: SALICYLIC ACID 17 g/100 mL
INACTIVE INGREDIENTS: GLYCERIN; PODOFILOX; BORNEOL; POLYETHYLENE GLYCOL, UNSPECIFIED; WATER

85578-006 Goodnites Skin tag and wart remover

ACTIVE INGREDIENT

Salicylic Acid 17%

PURPOSE

Skin tag and wart remover

INDICATIONS AND USAGE

For the removal of common and plantar warts
the common wart is easily recognized by the rough"cauliflower-likeappearance of the surface
the plantar wart is recognized by its location only on the bottom of the foot,its tenderness and the interruption of the footprint pattern

WARNINGS

For external use only

DO NOT USE

on irritated, infected, or reddened skin
on genital warts or warts on the face
if you have diabetes or poor blood circulation

do not use near eyes or mucous membranes
some mild irritation may occur
if excessive irritation occurs, stop use and consult a doctor

STOP USE

condition worsens
excessive irritation develops
you experience unexpected side effects

KEEP OUT OF REACH OF CHILDREN

lf swallowed, get medical help or contact a Poison Control Center right away

DOSAGE AND ADMINISTRATION

Clean affected area
Apply a thin layer to skin tag using applicator
Allow to dry fully
Repeat application twice daily for up to 4 weeks or as directed by a doctor

INACTIVE INGREDIENT

BORNEOL
GLYCERIN
PODOFILOX
POLYETHYLENE GLYCOL, UNSPECIFIED
WATER